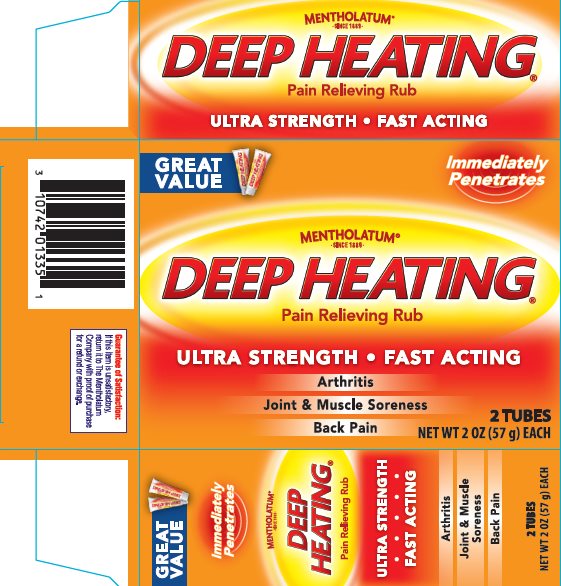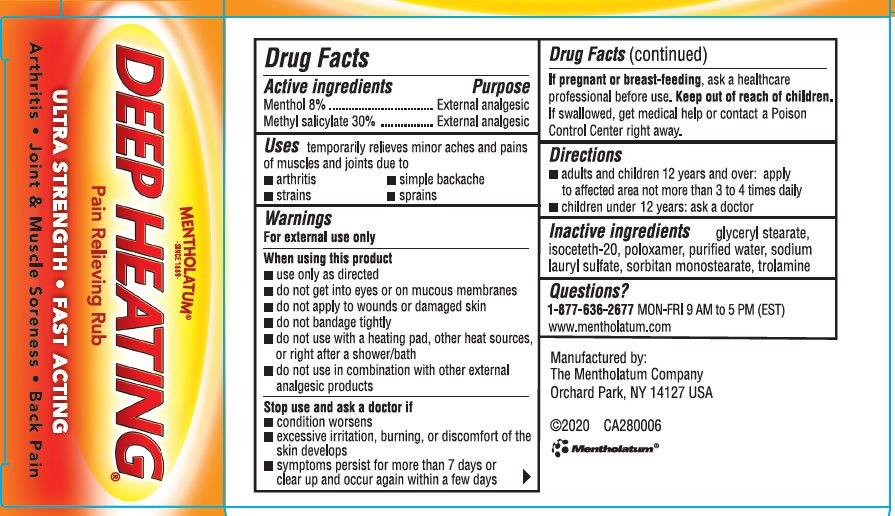 DRUG LABEL: Mentholatum Deep Heating Rub
NDC: 10742-2002 | Form: CREAM
Manufacturer: The Mentholatum Company
Category: otc | Type: HUMAN OTC DRUG LABEL
Date: 20241213

ACTIVE INGREDIENTS: MENTHOL, UNSPECIFIED FORM 80 mg/1 g; METHYL SALICYLATE 300 mg/1 g
INACTIVE INGREDIENTS: GLYCERYL MONOSTEARATE; ISOCETETH-20; POLOXAMER 407; WATER; SODIUM LAURYL SULFATE; SORBITAN MONOSTEARATE; TROLAMINE

Drug Facts - Mentholatum Deep Heating Rub

Active ingredients

Menthol 8%

Methyl salicylate 30%

Purpose

Menthol - External analgesic

Methyl salicylate - External analgesic

Uses

temporarily relieves minor aches and pains of muscles and joints due to

- arthritis
- strains
- simple backache
- sprains

Warnings

For external use only

When using this product

- use only as directed
- do not get into eyes or on mucous membranes
- do not apply to wounds or damaged skin
- do not bandage tightly
- do not use with heating pad, other heat sources, or right after a shower/bath
- do not use in combination with other external analgesic products

Stop use and ask a doctor if

- condition worsens
- excessive irritation, burning, or discomfort of the skin develops
- symptoms persist for more than 7 days or clear up and occur again within a few days

If pregnant or breast-feeding, ask a healthcare professional before use.

Keep out of reach of children.

If swallowed, get medical help or contact a Poison Control Center right away.

Directions

- adults and children 2 years and over: apply to affected area not more than 3 to 4 times daily
- children under 2 years: ask a doctor

Inactive ingredients

glyceryl stearate, isoceteh-20, poloxamer, purified water, sodium lauryl sulfate, sorbitan monostearate, trolamine

Questions?

1-877-636-2677 MON-FRI 9 AM to 5 PM (EST)

www.mentholatum.com